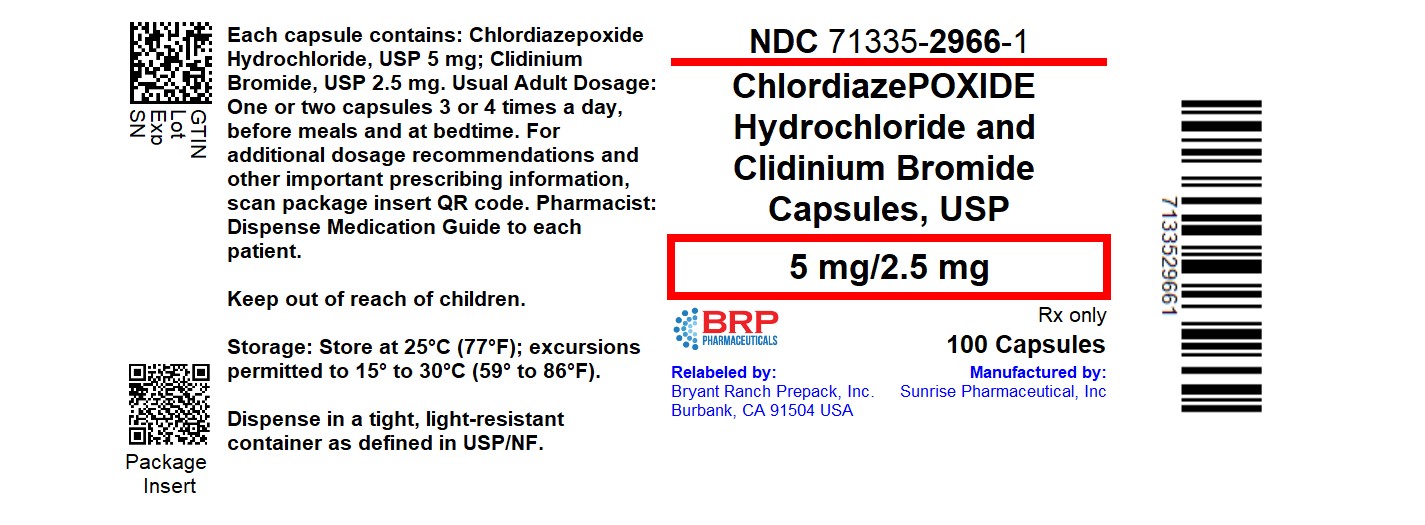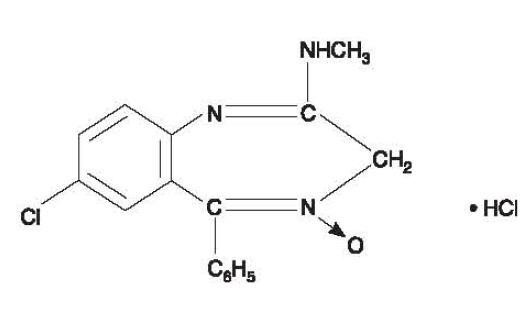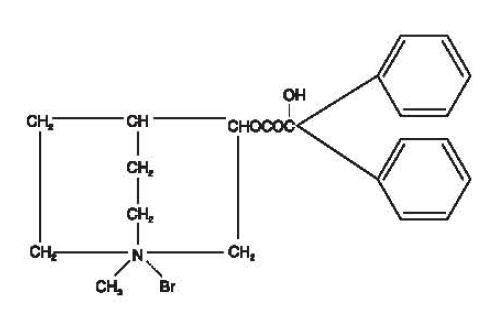 DRUG LABEL: Chlordiazepoxide Hydrochloride and Clidinium Bromide
NDC: 71335-2966 | Form: CAPSULE
Manufacturer: Bryant Ranch Prepack
Category: prescription | Type: HUMAN PRESCRIPTION DRUG LABEL
Date: 20260108
DEA Schedule: CIV

ACTIVE INGREDIENTS: CHLORDIAZEPOXIDE HYDROCHLORIDE 5 mg/1 1; CLIDINIUM BROMIDE 2.5 mg/1 1
INACTIVE INGREDIENTS: STARCH, CORN; LACTOSE MONOHYDRATE; TALC; D&C YELLOW NO. 10; FD&C GREEN NO. 3; TITANIUM DIOXIDE; GELATIN, UNSPECIFIED

Chlordiazepoxide Hydrochloride and Clidinium Bromide Capsules, USP for oral use

WARNING: RISKS FROM CONCOMITANT USE WITH OPIOIDS; ABUSE, MISUSE, AND ADDICTION; and DEPENDENCE AND WITHDRAWAL REACTIONS

• Concomitant use of benzodiazepines and opioids may result in profound sedation, respiratory depression, coma, and death. Reserve concomitant prescribing of these drugs in patients for whom alternative treatment options are inadequate. Limit dosages and durations to the minimum required. Follow patients for signs and symptoms of respiratory depression and sedation (see WARNINGS and PRECAUTIONS and PRECAUTIONS, Drug Interactions).

• The use of benzodiazepines, including chlodiazepoxide hydrochloride, a component of Chlordiazepoxide Hydrochloride and Clidinium Bromide Capsules, exposes users to risks of abuse, misuse, and addiction, which can lead to overdose or death. Abuse and misuse of benzodiazepines commonly involve concomitant use of other medications, alcohol, and/or illicit substances, which is associated with an increased frequency of serious adverse outcomes. Before prescribing Chlordiazepoxide Hydrochloride and Clidinium Bromide Capsules and throughout treatment, assess each patient’s risk for abuse, misuse, and addiction (see WARNINGS).

• The continued use of benzodiazepines, including Chlordiazepoxide Hydrochloride and Clidinium Bromide Capsules, may lead to clinically significant physical dependence. The risks of dependence and withdrawal increase with longer treatment duration and higher daily dose. Abrupt discontinuation or rapid dosage reduction of Chlordiazepoxide Hydrochloride and Clidinium Bromide Capsules after continued use may precipitate acute withdrawal reactions, which can be life-threatening. To reduce the risk of withdrawal reactions, use a gradual taper to discontinue Chlordiazepoxide Hydrochloride and Clidinium Bromide Capsules or reduce the dosage (see WARNINGS and DOSAGE AND ADMINISTRATION).

DESCRIPTION

Chlordiazepoxide Hydrochloride and Clidinium Bromide Capsules is a fixed-combination of chlordiazepoxide hydrochloride, a benzodiazepine, and clidinium bromide, an anticholinergic.

Each Chlordiazepoxide Hydrochloride and Clidinium Bromide capsule contains the active ingredients 5 mg chlordiazepoxide hydrochloride and 2.5 mg clidinium bromide. Each capsule also contains the inactive ingredients corn starch, lactose monohydrate, talc, D&C Yellow No. 10, FD&C Green No. 3, titanium dioxide, and gelatin.

Chlordiazepoxide hydrochloride is 7-chloro-2-methylamino-5-phenyl-3H-1,4-benzodiazepine 4-oxide hydrochloride. A colorless, crystalline substance, it is soluble in water. It is unstable in solution and the powder must be protected from light. The molecular weight is 336.22. The structural formula of chlordiazepoxide hydrochloride is as follows:

Clidinium bromide is a synthetic anticholinergic agent which has been shown in experimental and clinical studies to have a antispasmodic and antisecretory effect on the gastrointestinal tract. Structurally clidinium bromide is:

ANIMAL PHARMACOLOGY

Chlordiazepoxide hydrochloride has been studied extensively in many species of animals and these studies are suggestive of action on the limbic system of the brain, which recent evidence indicates is involved in emotional responses. Hostile monkeys were made tame by oral drug doses, which did not cause sedation. Chlordiazepoxide hydrochloride revealed a "taming-action with the elimination of fear and aggression”. The taming effect of chlordiazepoxide hydrochloride was further demonstrated in rats made vicious by lesions in the septal area of the brain. The drug dosage which effectively blocked the vicious reaction was well below the dose which caused sedation in these animals.

The oral LD50 of single doses of chlordiazepoxide hydrochloride, calculated according to the method of Miller and Tainter, is 720 ± 51 mg/kg as determined in mice observed over a period of 5 days following dosage.

Clidinium bromide is an effective anticholinergic agent with activity approximating that of atropine sulfate against acetylcholine-induced spasms in isolated intestinal strips. On oral administration in mice, it proved an effective antisialagogue in preventing pilocarpine-induced salivation. Spontaneous intestinal motility in both rats and dogs is reduced following oral dosing with 0.1 to 0.25 mg/kg. Potent cholinergic ganglionic blocking effects (vagal) were produced with intravenous usage in anesthetized dogs.

Oral doses of 2.5 mg/kg to dogs produced signs of nasal dryness and slight pupillary dilation. In two other species, monkeys and rabbits, doses of 5 mg/kg, po, given three times daily for 5 days did not produce apparent secretory or visual changes.

The oral LD50 of single doses of clidinium bromide is 860 ± 57 mg/kg as determined in mice observed over a period of 5 days following dosage; the calculations were made according to the method of Miller and Tainter.

Effects on Reproduction

Reproduction studies in rats fed chlordiazepoxide hydrochloride, 10, 20 and 80 mg/kg daily, and bred through one or two matings showed no congenital anomalies, nor were there adverse effects on lactation of the dams or growth of the newborn. However, in another study at 100 mg/kg daily there was noted a significant decrease in the fertilization rate and a marked decrease in the viability and body weight of offspring which may be attributable to sedative activity, thus resulting in lack of interest in mating and lessened maternal nursing and care of the young. One neonate in each of the first and second matings in the rat reproduction study at the 100 mg/kg dose exhibited major skeletal defects. Further studies are in progress to determine the significance of these findings.

Two series of reproduction experiments with clidinium bromide were carried out in rats, employing dosages of 2.5 and 10 mg/kg daily in each experiment. In the first experiment, clidinium bromide was administered for a 9-week interval prior to mating; no untoward effect on fertilization or gestation was noted. The offspring were taken by caesarean section and did not show a significant incidence of congenital anomalies when compared to control animals. In the second experiment, adult animals were given clidinium bromide for 10 days prior to and through two mating cycles. No significant effects were observed on fertility, gestation, viability of offspring or lactation, as compared to control animals, nor was there a significant incidence of congenital anomalies in the offspring derived from these experiments.

A reproduction study of Chlordiazepoxide Hydrochloride and Clidinium Bromide Capsules was carried out in rats through two successive matings. Oral daily doses were administered in two concentrations: 2.5 mg/kg chlordiazepoxide hydrochloride with 1.25 mg/kg clidinium bromide or 25 mg/kg chlordiazepoxide hydrochloride with 12.5 mg/kg clidinium bromide. In the first mating, no significant differences were noted between the control or the treated groups, with the exception of a slight decrease in the number of animals surviving during lactation among those receiving the highest dosage. As with all anticholinergic drugs, an inhibiting effect on lactation may occur. In the second mating, similar results were obtained except for a slight decrease in the number of pregnant females and in the percentage of offspring surviving until weaning. No congenital anomalies were observed in both matings in either the control or treated groups. Additional animal reproduction studies are in progress.

INDICATIONS AND USAGE

Chlordiazepoxide Hydrochloride and Clidinium Bromide Capsules are indicated to control emotional and somatic factors in gastrointestinal disorders. Chlordiazepoxide Hydrochloride and Clidinium Bromide Capsules may also be used as adjunctive therapy in the treatment of peptic ulcer and in the treatment of the irritable bowel syndrome (irritable colon, spastic colon, mucous colitis) and acute enterocolitis.

CONTRAINDICATIONS

Chlordiazepoxide Hydrochloride and Clidinium Bromide Capsules are contraindicated in the presence of glaucoma (since the anticholinergic component may produce some degree of mydriasis) and in patients with prostatic hypertrophy and benign bladder neck obstruction. It is contraindicated in patients with known hypersensitivity to chlordiazepoxide hydrochloride and/or clidinium bromide.

WARNINGS

Risks From Concomitant Use with Opioids

Concomitant use of benzodiazepines, including Chlordiazepoxide Hydrochloride and Clidinium Bromide Capsules, and opioids may result in profound sedation, respiratory depression, coma, and death. Because of these risks, reserve concomitant prescribing of these drugs - in patients for whom alternative treatment options are inadequate.

Observational studies have demonstrated that concomitant use of opioid analgesics and benzodiazepines increases the risk of drug-related mortality compared to use of opioids alone. If a decision is made to prescribe Chlordiazepoxide Hydrochloride and Clidinium Bromide Capsules concomitantly with opioids, prescribe the lowest effective dosages and minimum durations of concomitant use, and follow patients closely for signs and symptoms of respiratory depression and sedation. Advise both patients and caregivers about the risks of respiratory depression and sedation when Chlordiazepoxide Hydrochloride and Clidinium Bromide Capsules are used with opioids (see PRECAUTIONS).

Abuse, Misuse, and Addiction

The use of benzodiazepines, including chlordiazepoxide hydrochloride, a component of Chlordiazepoxide Hydrochloride and Clidinium Bromide Capsules, exposes users to the risks of abuse, misuse, and addiction, which can lead to overdose or death. Abuse and misuse of benzodiazepines often (but not always) involve the use of doses greater than the maximum recommended dosage and commonly involve concomitant use of other medications, alcohol, and/or illicit substances, which is associated with an increased frequency of serious adverse outcomes, including respiratory depression, overdose, or death (see DRUG ABUSE AND DEPENDENCE).

Before prescribing Chlordiazepoxide Hydrochloride and Clidinium Bromide Capsules and throughout treatment, assess each patient’s risk for abuse, misuse, and addiction (e.g., using a standardized screening tool). Use of Chlordiazepoxide Hydrochloride and Clidinium Bromide Capsules, particularly in patients at elevated risk, necessitates counseling about the risks and proper use of Chlordiazepoxide Hydrochloride and Clidinium Bromide Capsules along with monitoring for signs and symptoms of abuse, misuse, and addiction. Prescribe the lowest effective dosage; avoid or minimize concomitant use of CNS depressants and other substances associated with abuse, misuse, and addiction (e.g., opioid analgesics, stimulants); and advise patients on the proper disposal of unused drug. If a substance use disorder is suspected, evaluate the patient and institute (or refer them for) early treatment, as appropriate.

Dependence and Withdrawal Reactions

To reduce the risk of withdrawal reactions, use a gradual taper to discontinue Chlordiazepoxide Hydrochloride and Clidinium Bromide Capsules or reduce the dosage (a patient-specific plan should be used to taper the dosage) (see DOSAGE AND ADMINISTRATION).

Patients at an increased risk of withdrawal adverse reactions after benzodiazepine discontinuation or rapid dosage reduction include those who take higher dosages, and those who have had longer durations of use.

Acute Withdrawal Reactions

The continued use of benzodiazepines, including Chlordiazepoxide Hydrochloride and Clidinium Bromide Capsules, may lead to clinically significant physical dependence. Abrupt discontinuation or rapid dosage reduction of Chlordiazepoxide Hydrochloride and Clidinium Bromide Capsules after continued use, or administration of flumazenil (a benzodiazepine antagonist) may precipitate acute withdrawal reactions, which can be life-threatening (e.g., seizures) (see DRUG ABUSE AND DEPENDENCE).

Protracted Withdrawal Syndrome

In some cases, benzodiazepine users have developed a protracted withdrawal syndrome with withdrawal symptoms lasting weeks to more than 12 months (see DRUG ABUSE AND DEPENDENCE).

Effects on the Ability to Drive or Operate Machinery

As in the case of other preparations containing CNS-acting drugs, patients receiving Chlordiazepoxide Hydrochloride and Clidinium Bromide Capsules should be cautioned about possible combined effects with opioids, alcohol and other CNS depressants. For the same reason, they should be cautioned against hazardous occupations requiring complete mental alertness, such as operating machinery or driving a motor vehicle.

Usage In Pregnancy

An increased risk of congenital malformations associated with the use of minor tranquilizers (chlordiazepoxide, diazepam and meprobamate) during the first trimester of pregnancy has been suggested in several studies. Because use of these drugs is rarely a matter of urgency, their use during this period should almost always be avoided. The possibility that a woman of childbearing potential may be pregnant at the time of institution of therapy should be considered. Patients should be advised that if they become pregnant during therapy or intend to become pregnant they should communicate with their physicians about the desirability of discontinuing the drug.

As with all anticholinergic drugs, an inhibiting effect on lactation may occur (see ANIMAL PHARMACOLOGY).

OVERDOSAGE

Manifestations of chlordiazepoxide hydrochloride overdosage include somnolence, confusion, coma and diminished reflexes. Respiration, pulse and blood pressure should be monitored, as in all cases of drug overdosage, although, in general, these effects have been minimal following chlordiazepoxide hydrochloride overdosage.

While the signs and symptoms of Chlordiazepoxide Hydrochloride and Clidinium Bromide Capsules overdosage may be produced by either of its components, usually such symptoms will be overshadowed by the anticholinergic actions of clidinium bromide. The symptoms of overdosage of clidinium bromide are excessive dryness of mouth, blurring of vision, urinary hesitancy and constipation.

General supportive measures should be employed, along with immediate gastric lavage. Administer physostigmine 0.5 to 2 mg at a rate of no more than 1 mg per minute. This may be repeated in 1 to 4 mg doses if arrhythmias, convulsions or deep coma recur. Intravenous fluids should be administered and an adequate airway maintained. Hypotension may be combated by the use of levarterenol or metaraminol. Methylphenidate or caffeine and sodium benzoate may be given to combat CNS-depressive effects. Dialysis is of limited value. Should excitation occur, barbiturates should not be used. As with the management of intentional overdosage with any drug, it should be borne in mind that multiple agents may have been ingested.

Withdrawal symptoms of the barbiturate type have occurred after the discontinuation of benzodiazepines (see DRUG ABUSE AND DEPENDENCE).

PRECAUTIONS

CNS Adverse Reactions

In geriatric or debilitated patients, it is recommended that the dosage be limited to the smallest effective amount to preclude the development of ataxia, oversedation or confusion (not more than 2 Chlordiazepoxide Hydrochloride and Clidinium Bromide capsules per day initially, to be increased gradually as needed and tolerated). In general, the concomitant administration of Chlordiazepoxide Hydrochloride and Clidinium Bromide Capsules and other psychotropic agents is not recommended. If such combination therapy seems indicated, careful consideration should be given to the pharmacology of the agents to be employed — particularly when the known potentiating compounds such as the MAO inhibitors and phenothiazines are to be used. The usual precautions in treating patients with impaired renal or hepatic function should be observed.

Paradoxical reactions to chlordiazepoxide hydrochloride, e.g., excitement, stimulation and acute rage, have been reported in psychiatric patients and should be watched for during Chlordiazepoxide Hydrochloride and Clidinium Bromide Capsules therapy. The usual precautions are indicated when chlordiazepoxide hydrochloride is used in the treatment of anxiety states where there is any evidence of impending depression; it should be borne in mind that suicidal tendencies may be present and protective measures may be necessary.

Information for Patients

Abuse, Misuse, and Addiction

Inform patients that the use of Chlordiazepoxide Hydrochloride and Clidinium Bromide Capsules, even at recommended dosages, exposes users to risks of abuse, misuse, and addiction, which can lead to overdose and death, especially when used in combination with other medications (e.g., opioid analgesics), alcohol, and/or illicit substances. Inform patients about the signs and symptoms of benzodiazepine abuse, misuse, and addiction; to seek medical help if they develop these signs and/or symptoms; and on the proper disposal of unused drug (see WARNINGS).

Withdrawal Reactions

Inform patients that the continued use of Chlordiazepoxide Hydrochloride and Clidinium Bromide Capsules may lead to clinically significant physical dependence and that abrupt discontinuation or rapid dosage reduction of Chlordiazepoxide Hydrochloride and Clidinium Bromide Capsules may precipitate acute withdrawal reactions, which can be life-threatening. Inform patients that in some cases, patients taking benzodiazepines have developed a protracted withdrawal syndrome with withdrawal symptoms lasting weeks to more than 12 months. Instruct patients that discontinuation or dosage reduction of Chlordiazepoxide Hydrochloride and Clidinium Bromide Capsules may require a slow taper (see WARNINGSand DRUG ABUSE AND DEPENDENCE).

Concomitant Use With Opioids and Other CNS Depressants

Inform patients and caregivers that potentially fatal additive effects may occur if Chlordiazepoxide Hydrochloride and Clidinium Bromide Capsules is used with opioids or other CNS depressants, including alcohol, and not to use these concomitantly unless supervised by a health care provider (see WARNINGS and PRECAUTIONS, Drug Interactions).

Drug Interactions

Opioids

The concomitant use of benzodiazepines, including chlordiazepoxide hydrochloride, a component of Chlordiazepoxide Hydrochloride and Clidinium Bromide Capsules, and opioids increases the risk of respiratory depression because of actions at different receptor sites in the CNS that control respiration.

Benzodiazepines interact at GABAA sites and opioids interact primarily at mu receptors. When benzodiazepines and opioids are combined, the potential for benzodiazepines to significantly worsen opioid-related respiratory depression exists. Limit dosage and duration of concomitant use of Chlordiazepoxide Hydrochloride and Clidinium Bromide Capsules and opioids, and follow patients closely for respiratory depression and sedation.

Oral Anticoagulants

Although clinical studies have not established a cause and effect relationship, physicians should be aware that variable effects on blood coagulation have been reported very rarely in patients receiving oral anticoagulants and chlordiazepoxide hydrochloride, a component of Chlordiazepoxide Hydrochloride and Clidinium Bromide Capsules.

Pediatric Use

Safety and effectiveness in pediatric patients have not been established.

Geriatric Use

Geriatric subjects may be particularly prone to experiencing drowsiness, ataxia and confusion while receiving Chlordiazepoxide Hydrochloride and Clidinium Bromide Capsules. These effects can usually be avoided with proper dosage adjustment, although they have occasionally been observed even at the lower dosage ranges. Dosing in geriatric subjects should be initiated cautiously (no more than 2 capsules per day) and increased gradually if needed and tolerated (see DOSAGE AND ADMINISTRATION). Chlordiazepoxide Hydrochloride and Clidinium Bromide Capsules are contraindicated in the presence of glaucoma, prostatic hypertrophy and benign bladder neck obstruction (see CONTRAINDICATIONS).

ADVERSE REACTIONS

No side effects or manifestations not seen with either compound alone have been reported with the administration of Chlordiazepoxide Hydrochloride and Clidinium Bromide Capsules. However, since Chlordiazepoxide Hydrochloride and Clidinium Bromide Capsules contain chlordiazepoxide hydrochloride and clidinium bromide, the possibility of untoward effects which may be seen with either of these two compounds cannot be excluded.

When chlordiazepoxide hydrochloride has been used alone the necessity of discontinuing therapy because of undesirable effects has been rare. Drowsiness, ataxia and confusion have been reported in some patients — particularly the elderly and debilitated. While these effects can be avoided in almost all instances by proper dosage adjustment, they have occasionally been observed at the lower dosage ranges. In a few instances syncope has been reported.

Other adverse reactions reported during therapy with chlordiazepoxide hydrochloride include isolated instances of skin eruptions, edema, minor menstrual irregularities, nausea and constipation, extrapyramidal symptoms, as well as increased and decreased libido. Such side effects have been infrequent and are generally controlled with reduction of dosage. Changes in EEG patterns (low-voltage fast activity) have been observed in patients during and after chlordiazepoxide hydrochloride treatment.

Blood dyscrasias, including agranulocytosis, jaundice and hepatic dysfunction have occasionally been reported during therapy with chlordiazepoxide hydrochloride. When chlordiazepoxide hydrochloride treatment is protracted, periodic blood counts and liver function tests are advisable.

Adverse effects reported with use of Chlordiazepoxide Hydrochloride and Clidinium Bromide Capsules are those typical of anticholinergic agents, i.e., dryness of the mouth, blurring of vision, urinary hesitancy and constipation. Constipation has occurred most often when Chlordiazepoxide Hydrochloride and Clidinium Bromide Capsules therapy has been combined with other spasmolytic agents and/or a low residue diet.

To report SUSPECTED ADVERSE REACTIONS, contact Sunrise Pharmaceutical, Inc. at 732-382-6085 or FDA at 1-800-FDA-1088 or www.fda.gov/medwatch.

DRUG ABUSE AND DEPENDENCE

Controlled Substance

Chlordiazepoxide Hydrochloride and Clidinium Bromide Capsules contains chlordiazepoxide hydrochloride, a Schedule IV controlled substance and clidinium bromide, which is not a controlled substance. Chlordiazepoxide Hydrochloride and Clidinium Bromide Capsules is exempted from Schedule IV and is not controlled under the Controlled Substances Act.

Abuse

Chlordiazepoxide hydrochloride, a component of Chlordiazepoxide Hydrochloride and Clidinium Bromide Capsules, is a CNS depressant with a potential for abuse and addiction. Abuse is the intentional, non-therapeutic use of a drug, even once, for its desirable psychological or physiological effects. Misuse is the intentional use, for therapeutic purposes, of a drug by an individual in a way other than prescribed by a health care provider or for whom it was not prescribed. Drug addiction is a cluster of behavioral, cognitive, and physiological phenomena that may include a strong desire to take the drug, difficulties in controlling drug use (e.g., continuing drug use despite harmful consequences, giving a higher priority to drug use than other activities and obligations), and possible tolerance or physical dependence. Even taking benzodiazepines as prescribed may put patients at risk for abuse and misuse of their medication. Abuse and misuse of benzodiazepines may lead to addiction.

Abuse and misuse of benzodiazepines often (but not always) involve the use of doses greater than the maximum recommended dosage and commonly involve concomitant use of other medications, alcohol, and/or illicit substances, which is associated with an increased frequency of serious adverse outcomes, including respiratory depression, overdose, or death. Benzodiazepines are often sought by individuals who abuse drugs and other substances, and by individuals with addictive disorders (see WARNINGS).

The following adverse reactions have occurred with benzodiazepine abuse and/or misuse: abdominal pain, amnesia, anorexia, anxiety, aggression, ataxia, blurred vision, confusion, depression, disinhibition, disorientation, dizziness, euphoria, impaired concentration and memory, indigestion, irritability, muscle pain, slurred speech, tremors, and vertigo.

The following severe adverse reactions have occurred with benzodiazepine abuse and/or misuse: delirium, paranoia, suicidal ideation and behavior, seizures, coma, breathing difficulty, and death. Death is more often associated with polysubstance use (especially benzodiazepines with other CNS depressants such as opioids and alcohol).

Dependence

Physical Dependence

Chlordiazepoxide Hydrochloride and Clidinium Bromide Capsules may produce physical dependence from continued therapy. Physical dependence is a state that develops as a result of physiological adaptation in response to repeated drug use, manifested by withdrawal signs and symptoms after abrupt discontinuation or a significant dose reduction of a drug. Abrupt discontinuation or rapid dosage reduction of benzodiazepines or administration of flumazenil, a benzodiazepine antagonist, may precipitate acute withdrawal reactions, including seizures, which can be life-threatening. Patients at an increased risk of withdrawal adverse reactions after benzodiazepine discontinuation or rapid dosage reduction include those who take higher dosages (i.e., higher and/or more frequent doses) and those who have had longer durations of use (see WARNINGS).
To reduce the risk of withdrawal reactions, use a gradual taper to discontinue Chlordiazepoxide Hydrochloride and Clidinium Bromide Capsules or reduce the dosage (see WARNINGS and DOSAGE AND ADMININSTRATION).

Acute Withdrawal Signs and Symptoms

Acute withdrawal signs and symptoms associated with benzodiazepines have included abnormal involuntary movements, anxiety, blurred vision, depersonalization, depression, derealization, dizziness, fatigue, gastrointestinal adverse reactions (e.g., nausea, vomiting, diarrhea, weight loss, decreased appetite), headache, hyperacusis, hypertension, irritability, insomnia, memory impairment, muscle pain and stiffness, panic attacks, photophobia, restlessness, tachycardia, and tremor. More severe acute withdrawal signs and symptoms, including life-threatening reactions, have included catatonia, convulsions, delirium tremens, depression, hallucinations, mania, psychosis, seizures and suicidality.

Protracted Withdrawal Syndrome

Protracted withdrawal syndrome associated with benzodiazepines is characterized by anxiety, cognitive impairment, depression, insomnia, formication, motor symptoms (e.g., weakness, tremor, muscle twitches), paresthesia, and tinnitus that persists beyond 4 to 6 weeks after initial benzodiazepine withdrawal. Protracted withdrawal symptoms may last weeks to more than 12 months. As a result, there may be difficulty in differentiating withdrawal symptoms from potential re-emergence or continuation of symptoms for which the benzodiazepine was being used.

Tolerance

Tolerance to Chlordiazepoxide Hydrochloride and Clidinium Bromide Capsules may develop from continued therapy. Tolerance is a physiological state characterized by a reduced response to a drug after repeated administration (i.e., a higher dose of a drug is required to produce the same effect that was once obtained at a lower dose). Tolerance to the therapeutic effects of Chlordiazepoxide Hydrochloride and Clidinium Bromide Capsules may develop; however, little tolerance develops to the amnestic reactions and other cognitive impairments caused by benzodiazepines.

DOSAGE AND ADMINISTRATION

Recommended Dosage

Because of the varied individual responses to tranquilizers and anticholinergics, the optimum dosage of Chlordiazepoxide Hydrochloride and Clidinium Bromide Capsules vary with the diagnosis and response of the individual patient. The dosage, therefore, should be individualized for maximum beneficial effects. The usual maintenance dose is 1 or 2 capsules, 3 or 4 times a day administered before meals and at bedtime.

Recommended Geriatric Dosage

Dosage should be limited to the smallest effective amount to preclude the development of ataxia, oversedation or confusion. The initial dose should not exceed 2 Chlordiazepoxide Hydrochloride and Clidinium Bromide capsules per day, to be increased gradually as needed and tolerated. Elderly patients have an increased risk of dose-related adverse reactions (see PRECAUTIONS).

Discontinuation or Dosage Reduction of Chlordiazepoxide Hydrochloride and Clidinium Bromide Capsules

To reduce the risk of withdrawal reactions, use a gradual taper to discontinue Chlordiazepoxide Hydrochloride and Clidinium Bromide Capsules or reduce the dosage. If a patient develops withdrawal reactions, consider pausing the taper or increasing the dosage to the previous tapered dosage level. Subsequently decrease the dosage more slowly (see WARNINGS and DRUG ABUSE AND DEPENDENCE).

HOW SUPPLIED

Chlordiazepoxide Hydrochloride and Clidinium Bromide Capsules are available in light green opaque cap and light green opaque body containing 5 mg chlordiazepoxide hydrochloride and 2.5 mg clidinium bromide, in bottle of 100 (NDC 71335-2966-1), with black imprint “N36” on both the cap and body.

Store at 25°C (77°F); excursions permitted to 15° to 30°C (59° to 86°F).

Keep out of reach of children.
Dispense in a tight, light-resistant container as defined in USP/NF.

Repackaged/Relabeled by:
Bryant Ranch Prepack, Inc.
Burbank, CA 91504

MEDICATION GUIDE

Chlordiazepoxide Hydrochloride and Clidinium Bromide (klor dye az e POKS ide hahy druh klohr id & kli DI nee um broh myde) Capsules, USP for oral use

What is the most important information I should know about Chlordiazepoxide Hydrochloride and Clidinium Bromide Capsules?

- Chlordiazepoxide Hydrochloride and Clidinium Bromide Capsules contain a benzodiazepine medicine. Taking Chlordiazepoxide Hydrochloride and Clidinium Bromide Capsules with opioid medicines, alcohol, or other central nervous system (CNS) depressants (including street drugs) can cause severe drowsiness, breathing problems (respiratory depression), coma, and death. Get emergency help right away if any of the following happens:
  - shallow or slowed breathing
  - breathing stops (which may lead to the heart stopping)
  - excessive sleepiness (sedation)

Do not drive or operate heavy machinery until you know how taking Chlordiazepoxide Hydrochloride and Clidinium Bromide Capsules with opioids affect you.

- Risk of abuse, misuse, and addiction. There is a risk of abuse, misuse, and addiction with benzodiazepines, including Chlordiazepoxide Hydrochloride and Clidinium Bromide Capsules, which can lead to overdose or death.
  - Serious side effects including coma and death have happened in people who have abused or misused benzodiazepines, including Chlordiazepoxide Hydrochloride and Clidinium Bromide Capsules. These serious side effects may also include delirium, paranoia, suicidal thoughts or actions, seizures, and difficulty breathing. Call your healthcare provider or go to the nearest hospital emergency room right away if you get any of these serious side effects.
  - You can develop an addiction even if you take Chlordiazepoxide Hydrochloride and Clidinium Bromide Capsules as prescribed by your healthcare provider.
  - Take Chlordiazepoxide Hydrochloride and Clidinium Bromide Capsules exactly as your healthcare provider prescribed.
  - Do not share your Chlordiazepoxide Hydrochloride and Clidinium Bromide Capsules with other people.
  - Keep Chlordiazepoxide Hydrochloride and Clidinium Bromide Capsules in a safe place and away from children.
- Physical dependence and withdrawal reactions. Chlordiazepoxide Hydrochloride and Clidinium Bromide Capsules can cause physical dependence and withdrawal reactions.
  - Do not suddenly stop using Chlordiazepoxide Hydrochloride and Clidinium Bromide Capsules. Stopping Chlordiazepoxide Hydrochloride and Clidinium Bromide Capsules suddenly can cause serious and life-threatening side effects, including unusual movements, responses, or expressions, seizures, sudden and severe mental or nervous system changes, depression, seeing or hearing things that others do not see or hear, an extreme increase in activity or talking, losing touch with reality, and suicidal thoughts or actions. Call your healthcare provider or go to the nearest hospital emergency room right away if you get any of these symptoms.
  - Some people who suddenly stop benzodiazepines have symptoms that can last for several weeks to more than 12 months, including anxiety, trouble remembering, learning, or concentrating, depression, problems sleeping, feeling like insects are crawling under your skin, weakness, shaking, muscle twitches, burning or prickling feeling in your hands, arms, legs or feet, and ringing in your ears.
  - Physical dependence is not the same as drug addiction. Your healthcare provider can tell you more about the differences between physical dependence and drug addiction.
  - Do not take more Chlordiazepoxide Hydrochloride and Clidinium Bromide Capsules than prescribed or take Chlordiazepoxide Hydrochloride and Clidinium Bromide Capsules for longer than prescribed.

What are Chlordiazepoxide Hydrochloride and Clidinium Bromide Capsules?

- Chlordiazepoxide Hydrochloride and Clidinium Bromide Capsules are prescription medicine that is used with other therapies for the treatment of:
  - stomach (peptic) ulcers
  - irritable bowel syndrome (IBS)
  - inflammation of the colon called acute enterocolitis
- Chlordiazepoxide Hydrochloride and Clidinium Bromide Capsules contain the medicines chlordiazepoxide hydrochloride and clidinium bromide.
- Chlordiazepoxide Hydrochloride and Clidinium Bromide Capsules contains chlordiazepoxide hydrochloride that can be abused or lead to dependence. Keep Chlordiazepoxide Hydrochloride and Clidinium Bromide Capsules in a safe place to prevent misuse and abuse. Selling or giving away Chlordiazepoxide Hydrochloride and Clidinium Bromide Capsules may harm others. Tell your healthcare provider if you have abused or been dependent on alcohol, prescription medicines or street drugs.
- It is not known if Chlordiazepoxide Hydrochloride and Clidinium Bromide Capsules are safe and effective in children.

Do not take Chlordiazepoxide Hydrochloride and Clidinium Bromide Capsules if you:

- have glaucoma
- have an enlarged prostate
- have a blockage of your bladder that causes problems with urination
- are allergic to chlordiazepoxide hydrochloride or clidinium bromide

Before you take Chlordiazepoxide Hydrochloride and Clidinium Bromide Capsules, tell your healthcare provider about all of your medical conditions, including if you:

- have eye problems
- have problems urinating or emptying your bladder
- have coordination problems
- have kidney or liver problems
- have a history of depression, mental illness, or suicidal thoughts
- have a history of drug or alcohol abuse or addiction
- have bleeding problems
- are pregnant or plan to become pregnant. Chlordiazepoxide Hydrochloride and Clidinium Bromide Capsules may harm your unborn baby. Avoid taking Chlordiazepoxide Hydrochloride and Clidinium Bromide Capsules during the first trimester of pregnancy. Tell your healthcare provider right away if you become pregnant during treatment with Chlordiazepoxide Hydrochloride and Clidinium Bromide Capsules.
- are breastfeeding or plan to breastfeed. Chlordiazepoxide Hydrochloride and Clidinium Bromide may pass through your breast milk and may harm your baby. Talk to your healthcare provider about the best way to feed your baby if you take Chlordiazepoxide Hydrochloride and Clidinium Bromide Capsules. Chlordiazepoxide Hydrochloride and Clidinium Bromide Capsules may decrease the amount of breast milk your body makes.

Tell your healthcare provider about all the medicines you take, including prescription and over-the-counter medicines, vitamins, and herbal supplements.

Taking Chlordiazepoxide Hydrochloride and Clidinium Bromide Capsules with certain other medicines can cause side effects or affect how well Chlordiazepoxide Hydrochloride and Clidinium Bromide Capsules or the other medicines work.

Do not start or stop other medicines without talking to your healthcare provider.

Especially tell your healthcare provider if you:

- take a monoamine oxidase inhibitor (MAOI) medicine or an anti-psychotic medicine called phenothiazine.

How should I take Chlordiazepoxide Hydrochloride and Clidinium Bromide Capsules?

- Take Chlordiazepoxide Hydrochloride and Clidinium Bromide Capsules exactly as your healthcare provider tells you to take it.
- Your healthcare provider may change your dose of Chlordiazepoxide Hydrochloride and Clidinium Bromide Capsules if needed. Do not change your dose of Chlordiazepoxide Hydrochloride and Clidinium Bromide Capsules or suddenly stop taking Chlordiazepoxide Hydrochloride and Clidinium Bromide Capsules without talking with your healthcare provider.
- If you take too much Chlordiazepoxide Hydrochloride and Clidinium Bromide Capsules, call your healthcare provider or go to the nearest hospital emergency room right away.

What are the possible side effects of Chlordiazepoxide Hydrochloride and Clidinium Bromide Capsules?

Chlordiazepoxide Hydrochloride and Clidinium Bromide Capsules may cause serious side effects, including: See “What is the most important information I should know about Chlordiazepoxide Hydrochloride and Clidinium Bromide Capsules?”

- Chlordiazepoxide Hydrochloride and Clidinium Bromide Capsules can make you sleepy or dizzy and can slow your thinking and motor skills.
  - Do not drive, operate heavy machinery, or do other dangerous activities until you know how Chlordiazepoxide Hydrochloride and Clidinium Bromide Capsules affect you.
  - Do not drink alcohol or take other drugs that may make you sleepy or dizzy while taking Chlordiazepoxide Hydrochloride and Clidinium Bromide Capsules without first talking to your healthcare provider. When taken with alcohol or drugs that cause sleepiness or dizziness, Chlordiazepoxide Hydrochloride and Clidinium Bromide Capsules may make your sleepiness or dizziness much worse.

The most common side effects of Chlordiazepoxide Hydrochloride and Clidinium Bromide Capsules include:

- dry mouth
- blurred vision
- nausea
- constipation
- skin problems
- swelling
- irregular menstrual (periods) cycles
- increased and decreased desire for sex (libido)
- problems starting to urinate
- drowsiness, coordination problems, and confusion may happen, especially in people who are elderly or weak

These are not all the possible side effects of Chlordiazepoxide Hydrochloride and Clidinium Bromide Capsules.

Call your doctor for medical advice about side effects. You may report side effects to FDA at 1-800-FDA-1088.

How should I store Chlordiazepoxide Hydrochloride and Clidinium Bromide Capsules?

- Store Chlordiazepoxide Hydrochloride and Clidinium Bromide Capsules at room temperature 77°F (25°C).
- Keep Chlordiazepoxide Hydrochloride and Clidinium Bromide Capsules and all medicines out of the reach of children.

General information about the safe and effective use of Chlordiazepoxide Hydrochloride and Clidinium Bromide Capsules.

Medicines are sometimes prescribed for purposes other than those listed in a Medication Guide. Do not take Chlordiazepoxide Hydrochloride and Clidinium Bromide Capsules for a condition for which it was not prescribed. Do not give Chlordiazepoxide Hydrochloride and Clidinium Bromide Capsules to other people, even if they have the same symptoms that you have. It may harm them. You can ask your pharmacist or healthcare provider for information about Chlordiazepoxide Hydrochloride and Clidinium Bromide Capsules that is written for health professionals.

What are the ingredients in Chlordiazepoxide Hydrochloride and Clidinium Bromide Capsules?

Active ingredient: chlordiazepoxide hydrochloride and clidinium bromide

Inactive ingredients: corn starch, lactose and talc. Gelatin capsule shells may contain titanium dioxide with the following dye systems: D&C Yellow No. 10 and FD&C Green No. 3.

Manufactured by: Sunrise Pharmaceutical, Inc., Rahway, NJ 07065

For more information, go to www.sunrisepharma.com or contact Sunrise Pharmaceutical, Inc. at 732-382-6085.

This Medication Guide has been approved by the U.S. Food and Drug Administration.

Issued: 07/2021 5356/00

PACKAGE LABEL

Chlordia/Cllidium BR 5mg/2.5mg Cap #100